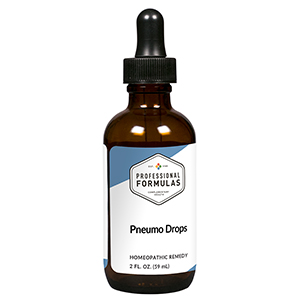 DRUG LABEL: Pneumo Drops
NDC: 63083-5018 | Form: LIQUID
Manufacturer: Professional Complementary Health Formulas
Category: homeopathic | Type: HUMAN OTC DRUG LABEL
Date: 20190815

ACTIVE INGREDIENTS: TEUCRIUM SCORODONIA FLOWERING TOP 2 [hp_X]/59 mL; EQUISETUM ARVENSE TOP 3 [hp_X]/59 mL; OENANTHE AQUATICA FRUIT 5 [hp_X]/59 mL; ARSENIC TRIIODIDE 6 [hp_X]/59 mL; BEEF LUNG 6 [hp_X]/59 mL; ANHYDROUS DIBASIC CALCIUM PHOSPHATE 10 [hp_X]/59 mL; TIN 10 [hp_X]/59 mL; ACTIVATED CHARCOAL 12 [hp_X]/59 mL; SILICON DIOXIDE 12 [hp_X]/59 mL; SULFUR 12 [hp_X]/59 mL
INACTIVE INGREDIENTS: ALCOHOL; WATER

HPD

ACTIVE INGREDIENTS

Teucrium scorodonia 2X
Equisetum arvense 3X
Phellandrium aquaticum 5X
Arsenicum iodatum 6X
Lung 6X
Calcarea phosphorica 10X
Stannum metallicum 10X
Carbo vegetabilis 12X
Silicea 12X
Sulphur 12X

QUESTIONS

Professional Formulas

PO Box 2034 Lake Oswego, OR 97035

INDICATIONS

For the temporary relief of shortness of breath, wheezing, cough, or fatigue.*

PURPOSE

*Claims based on traditional homeopathic practice, not accepted medical evidence. Not FDA evaluated.

WARNINGS

Consult a doctor if condition worsens or if symptoms persist. Keep out of the reach of children. In case of overdose, get medical help or contact a poison control center right away. If pregnant or breastfeeding, ask a healthcare professional before use.

Keep out of the reach of children.

PREGNANCY OR BREAST FEEDING

If pregnant or breastfeeding, ask a healthcare professional before use.

DIRECTIONS

Place drops under tongue 30 minutes before/after meals. Adults and children 12 years and over: Take 10 drops up to 3 times per day. Consult a physician for use in children under 12 years of age.

OTHER INFORMATION

Tamper resistant. If seal is broken, do not use. After opening, close container tightly and store at room temperature away from heat.

INACTIVE INGREDIENTS

20% ethanol, purified water.

LABEL

Est 1985

Professional Formulas

Complementary Health

Pneumo Drops

Homeopathic Remedy

2 FL. OZ. (59 mL)